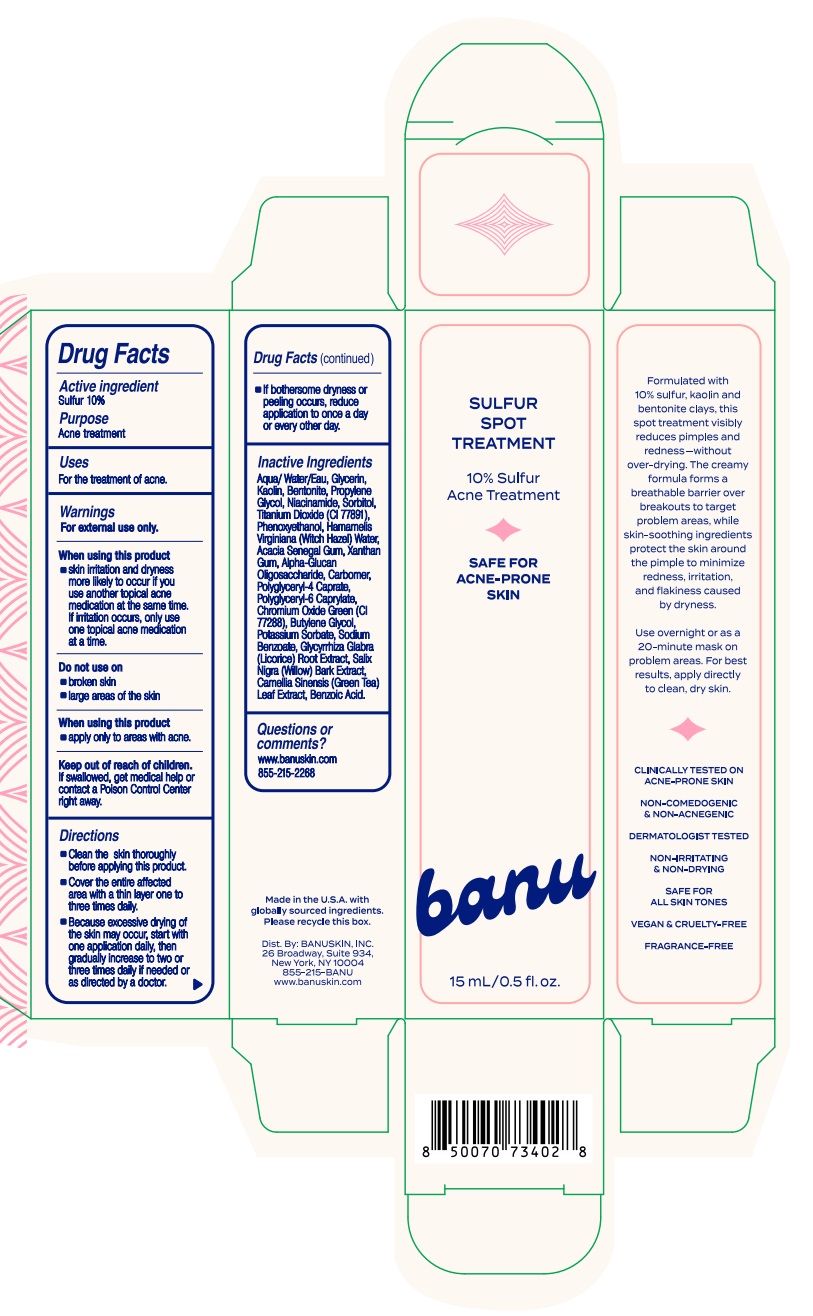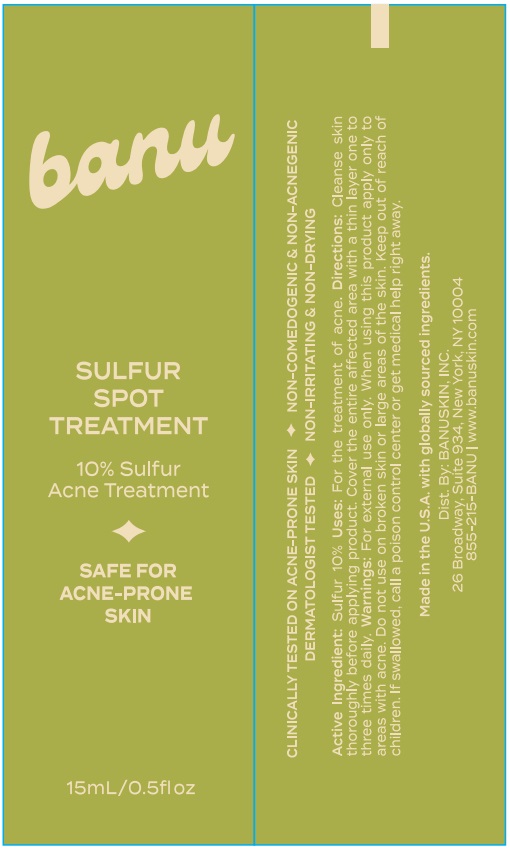 DRUG LABEL: Sulfur Spot Treatment
NDC: 85439-0102 | Form: CREAM
Manufacturer: Banuskin, Inc.
Category: otc | Type: HUMAN OTC DRUG LABEL
Date: 20250403

ACTIVE INGREDIENTS: SULFUR 10 g/100 mL
INACTIVE INGREDIENTS: POLYGLYCERYL-6 CAPRYLATE; BUTYLENE GLYCOL; SODIUM BENZOATE; BENZOIC ACID; CARBOMER; WATER; KAOLIN; BENTONITE; HAMAMELIS VIRGINIANA (WITCH HAZEL) LEAF WATER; XANTHAN GUM; CHROMIUM OXIDE GREENS; TITANIUM DIOXIDE; PHENOXYETHANOL; WILLOW BARK; CAMELLIA SINENSIS LEAF; ACACIA SENEGAL GUM; ALPHA-GLUCAN OLIGOSACCHARIDE; GLYCERIN; SORBITOL; PROPYLENE GLYCOL; NIACINAMIDE; POLYGLYCERYL-4 CAPRATE; POTASSIUM SORBATE; GLYCYRRHIZA GLABRA (LICORICE) ROOT POWDER

Sulfur Spot Treatment

Active Ingredients

Sulfur 10%

Purpose

Acne treatment

Uses

For the treatment of acne

Warnings

For external use only

When using this product

- skin irritation and dryness more likely to occur if you use another topical acne medication at the same time. If irritation occurs, only use one topical acne medication at a time.

Do not use on

- broken skin
- large areas of the skin

When using this product

- apply only to areas with acne

Keep out of reach of children.

If swallowed, get medical help or contact a Poison Control Center right away.

Directions

- Clean the skin thoroughly before applying this product.
- Cover the entire affected area with a thin layer one to three times daily.
- Because excessive drying of the skin may occur, start with one application daily, then gradually increase to two or three times daily if needed or as directed by a doctor.
- If bothersome dryness or peeling occurs, reduce application to once a day or every other day.

Inactive Ingredients

Aqua/Water/Eau, Glycerin, Kaolin, Bentonite, Propylene Glycol, Niacinamide, Sorbitol, Titanium Dioxide (Cl 77891), Phenoxyethanol, Hamamelis Virginiana (Witch Hazel) Water, Acacia Senegal Gum, Xanthan Gum, Alpha-Glucan Oligosaccharide, Carbomer, Poiyglyceryl-4 Caprate, Polyglyceryl-6 Caprylate, Chromium Oxide Green (Cl 77288), Butylene Glycol, Potassium Sorbate, Sodium Benzoate, Glycyrrhiza Glabra (Licorice) Root Extract, Salix Nigra (Willow) Bark Extract, Camellia Sinensis (Green Tea) Leaf Extract, Benzoic Acid.

Questions or comments?

www.banuskin.com

855-215-2268

Principal Display Panel

banu

SULFUR SPOT TREATMENT

10% Sulfur Acne Treatment

SAFE FOR ACNE-PRONE SKIN

15 mL/0.5 fl.oz.

DOSAGE AND ADMINISTRATION

Topical Cream

Label

15 mL Tube Carton

15 mL Tube